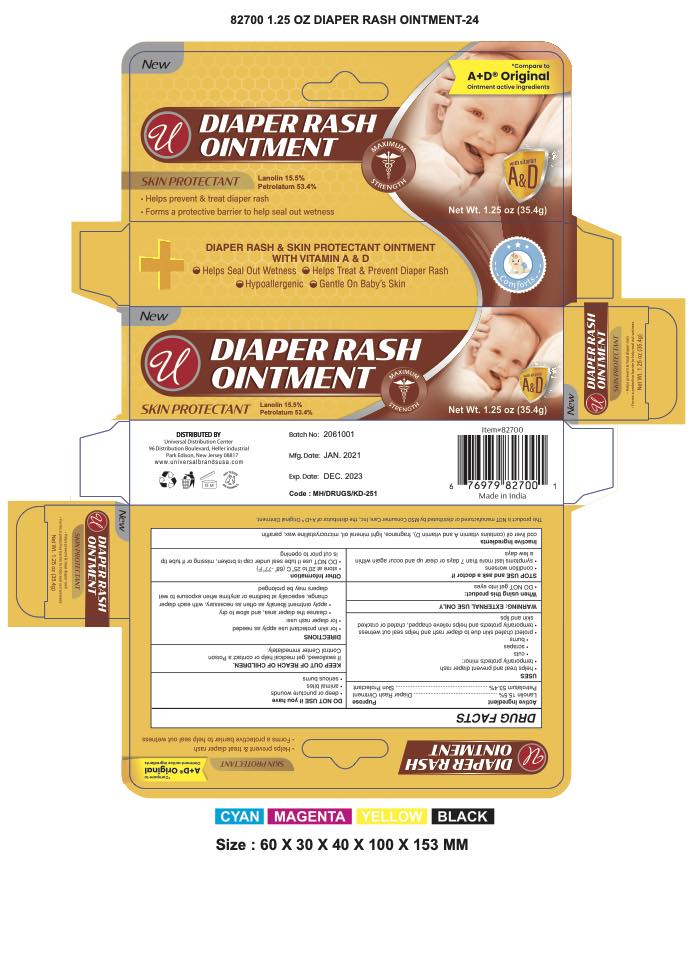 DRUG LABEL: Diaper Rash skin protectant
NDC: 52000-073 | Form: OINTMENT
Manufacturer: Universal Distribution Centre LLC
Category: otc | Type: HUMAN OTC DRUG LABEL
Date: 20251117

ACTIVE INGREDIENTS: LANOLIN 136.4 mg/1 g; PETROLATUM 469.9 mg/1 g
INACTIVE INGREDIENTS: COD LIVER OIL; LIGHT MINERAL OIL; MICROCRYSTALLINE WAX; PARAFFIN

Diaper Rash Ointment

Distributed by Bayer HealthCare LLC, Whippany, NJ, USA, 07981

ACTIVE INGREDIENT

Active ingredients | Purpose
Lanolin 15.5% | Diaper rash ointment
Petrolatum 53.4% | Skin Protectant

Uses

- helps treat and prevent diaper rash
- temporarily protects minor:
  - cuts
  - scrapes
  - burns
- temporarily protects and helps relieve chapped, chafed or cracked skin and lips
- protect chafed skin due to diaper rash and helps seal out wetness

Warnings

For external use only

When using this product

- do not get into eyes

Stop use and ask a doctor if

- condition worsens
- symptoms last more than 7 days or clear up and occur again within a few days

Do not use on

- deep or puncture wounds
- animal bites
- serious burns

Keep out of reach of children.If swallowed, get medical help or contact a Poison Control Center right away.

Directions

- for skin protectant useapply as needed
- for diaper rash use:
  - change wet and soiled diapers promptly
  - cleanse the diaper area, and allow to dry
  - apply ointment liberally as often as necessary, with each diaper change, especially at bedtime or anytime when exposure to wet diapers may be prolonged

Other information

store between 20°C to 25 °C (68° to 77°F)

Inactive Ingredients

cod liver oil (contains vitamin A & vitamin D), fragrance, light mineral oil, microcrystalline wax, paraffin